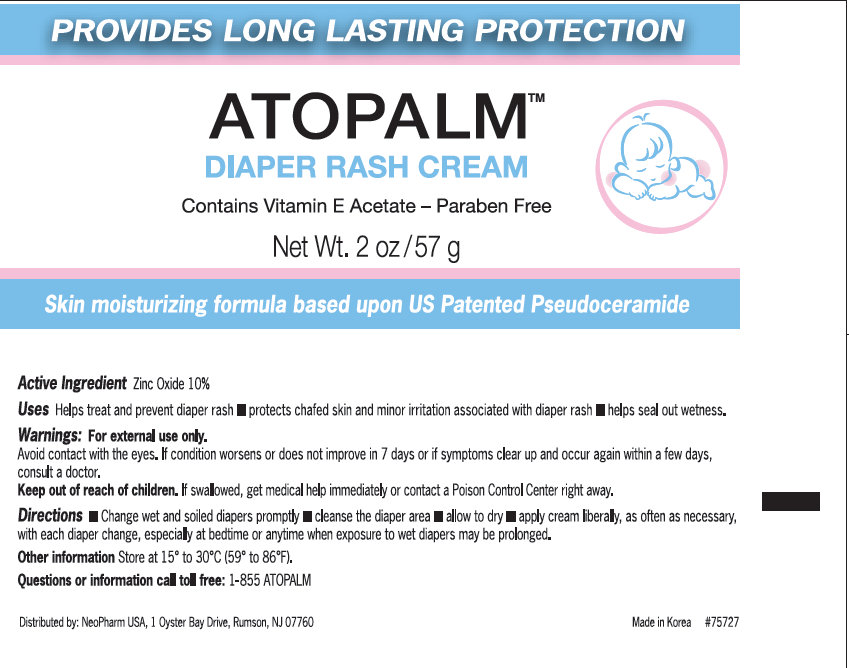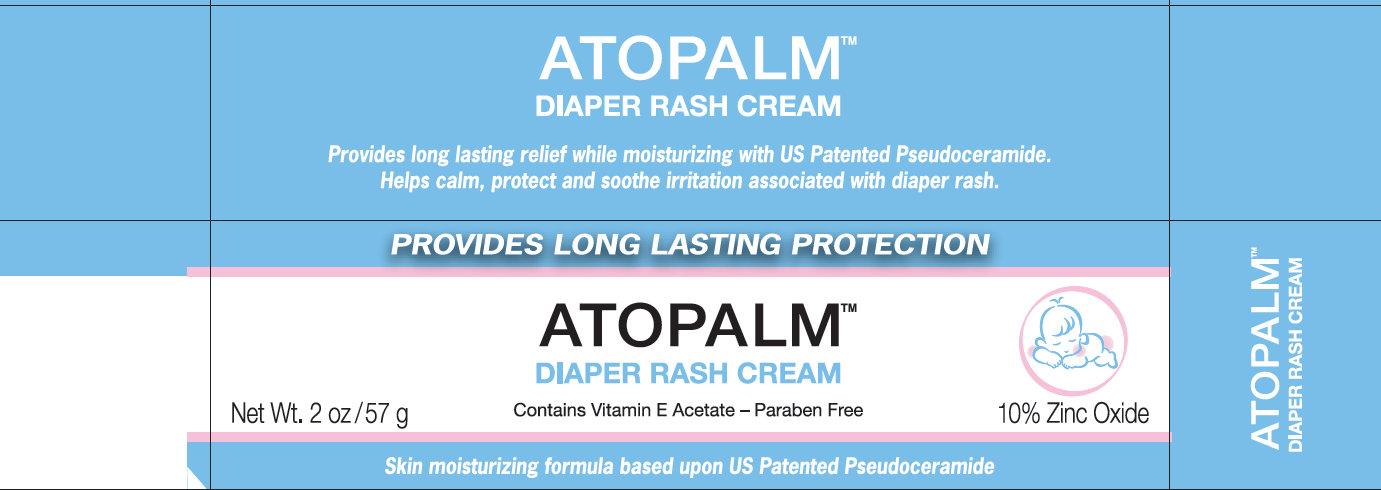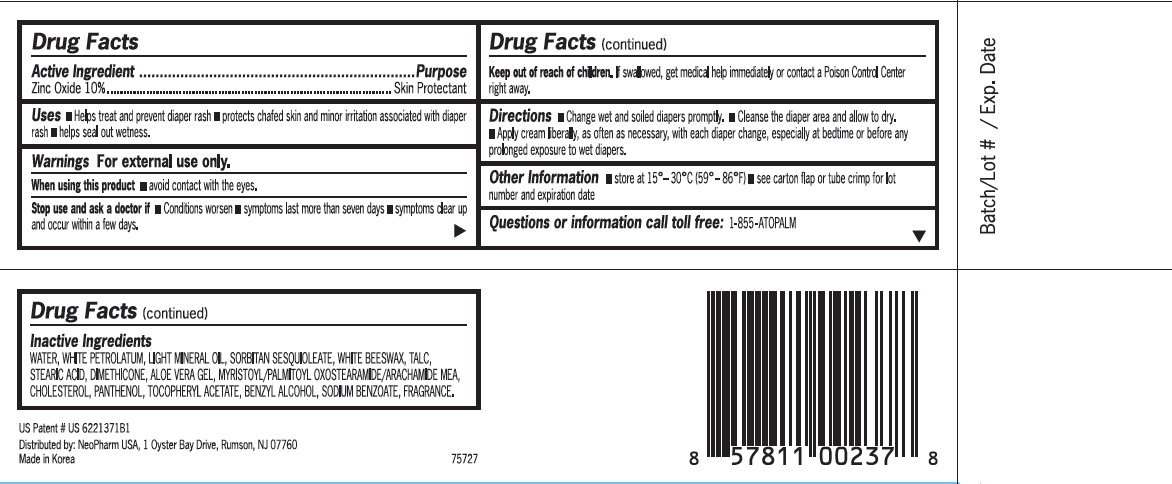 DRUG LABEL: ATOPALM Diaper Rash
NDC: 51141-0237 | Form: CREAM
Manufacturer: NeoPharm Co., Ltd
Category: otc | Type: HUMAN OTC DRUG LABEL
Date: 20120611

ACTIVE INGREDIENTS: ZINC OXIDE 10 g/100 g
INACTIVE INGREDIENTS: WATER; PETROLATUM; LIGHT MINERAL OIL; SORBITAN SESQUIOLEATE; WHITE WAX; TALC; STEARIC ACID; DIMETHICONE; ALOE VERA LEAF; MYRISTOYL/PALMITOYL OXOSTEARAMIDE/ARACHAMIDE MEA; CHOLESTEROL; PANTHENOL; .ALPHA.-TOCOPHEROL ACETATE; BENZYL ALCOHOL; SODIUM BENZOATE

ATOPALM Diaper Rash Cream

Active Ingredient

Zinc Oxide 10%

Purpose

Skin Protectant

Uses

- Helps treat and prevent diaper rash
- Protects chafed skin and minor irritation associated with diaper rash
- Helps seal out wetness.

Warnings

For external use only.

When using this product

- avoid contact with the eyes.

Stop use and ask a doctor if

- Conditions worsen
- symptoms last more than seven days
- symptoms clear up and occur within a few days.

Keep out of reach of children.

If swallowed, get medical help immediately or contact a Poison Control Center right away.

Directions

- Change wet and soiled promptly
- Cleanse the diaper area and allow to dry.
- Apply cream liberally, as often as necessary, with each diaper change, especially at bedtime or before any prolonged exposure to wet diapers.

Other Information

- store at 15 degrees - 30 degrees C (59 degrees - 86 degrees F)
- see carton flap or tube crimp for lot number and expiration date

Questions or information call toll free:

1-855-ATOPALM

Inactive Ingredients

WATER, WHITE PETROLATUM, LIGHT MINERAL OIL, SORBITAN SESQUILEATE, WHITE BEESWAX, TALC, STEARIC ACID, DIMETHICONE, ALOE VERA GEL, MYRISTOYL/PALMITOYL OXOSTEARAMIDE/ARACHAMIDE MEA, CHOLESTEROL, PANTHENOL, TOCOPHERYL ACETATE, BENZYL ALCOHOL, SODIUM BENZOATE, FRAGRANCE.